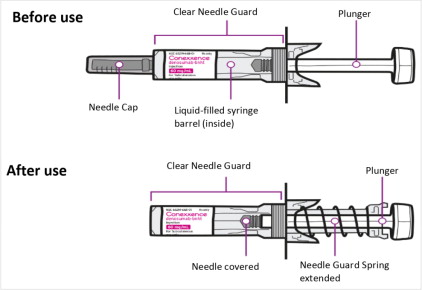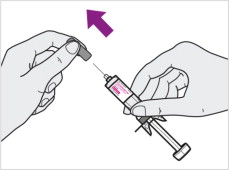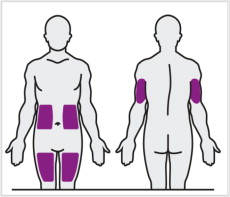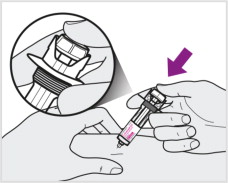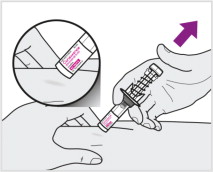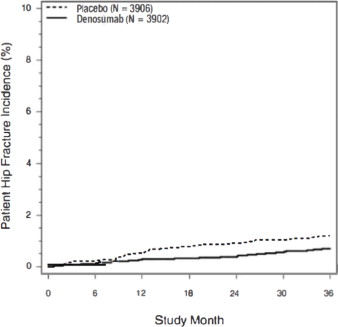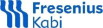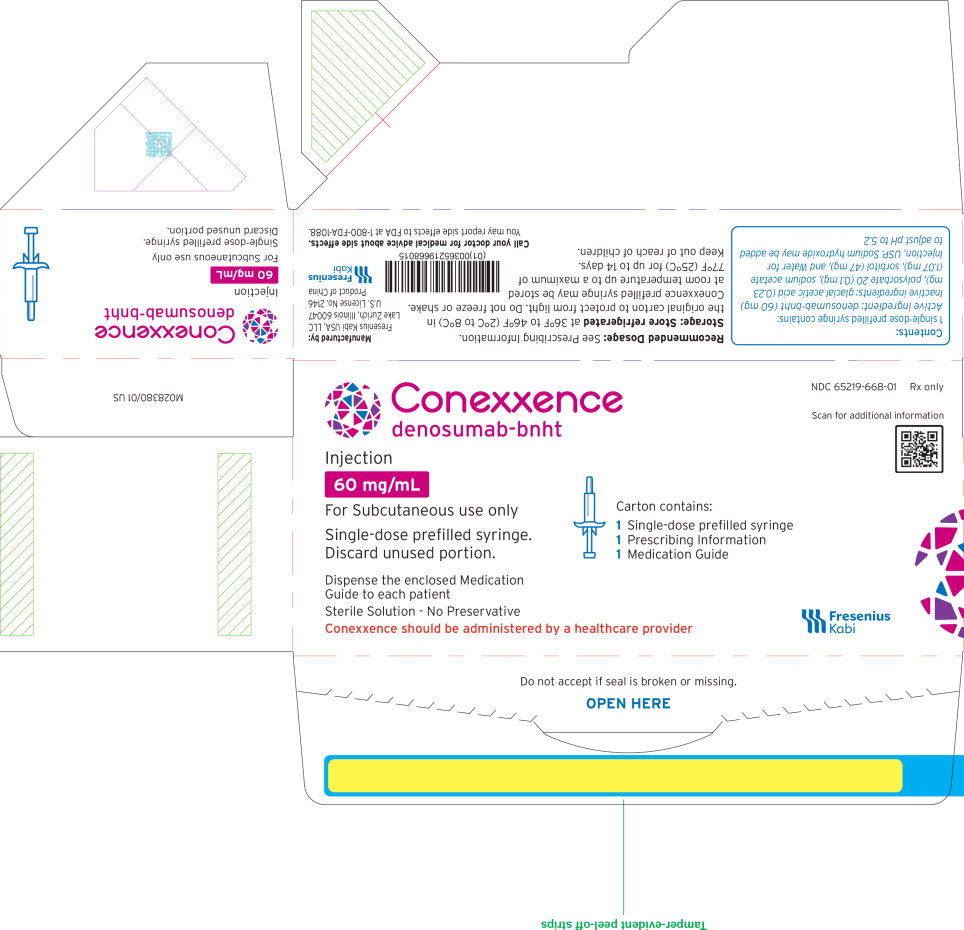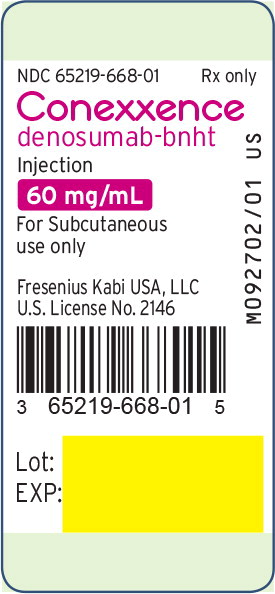 DRUG LABEL: CONEXXENCE
NDC: 65219-668 | Form: INJECTION
Manufacturer: Fresenius Kabi USA, LLC
Category: prescription | Type: HUMAN PRESCRIPTION DRUG LABEL
Date: 20251215

ACTIVE INGREDIENTS: Denosumab 60 mg/1 mL
INACTIVE INGREDIENTS: Sorbitol; Acetate Ion; Polysorbate 20; Water; Sodium Hydroxide

HIGHLIGHTS OF PRESCRIBING INFORMATION

These highlights do not include all the information needed to use CONEXXENCE safely and effectively. See full prescribing information for CONEXXENCE.
CONEXXENCE (denosumab-bnht) injection, for subcutaneous use
Initial U.S. Approval: 2025
CONEXXENCE (denosumab-bnht) is biosimilar [Biosimilar means that the biological product is approved based on data demonstrating that it is highly similar to an FDA-approved biological product, known as a reference product, and that there are no clinically meaningful differences between the biosimilar product and the reference product. Biosimilarity of CONEXXENCE has been demonstrated for the condition(s) of use (e.g., indication(s), dosing regimen(s)), strength(s), dosage form(s), and route(s) of administration described in its Full Prescribing Information.] to PROLIA® (denosumab).

WARNING: SEVERE HYPOCALCEMIA IN PATIENTS WITH ADVANCED KIDNEY DISEASE

See full prescribing information for complete boxed warning.

- Patients with advanced chronic kidney disease are at greater risk of severe hypocalcemia following denosumab products administration. Severe hypocalcemia resulting in hospitalization, life-threatening events and fatal cases have been reported. (5.1)
- The presence of chronic kidney disease-mineral bone disorder (CKD-MBD) markedly increases the risk of hypocalcemia. (5.1)
- Prior to initiating Conexxence in patients with advanced chronic kidney disease, evaluate for the presence of CKD-MBD. Treatment with Conexxence in these patients should be supervised by a healthcare provider with expertise in the diagnosis and management of CKD-MBD. (2.2), (5.1)

1 INDICATIONS AND USAGE

Conexxence is a RANK ligand (RANKL) inhibitor indicated for treatment:

- of postmenopausal women with osteoporosis at high risk for fracture (1.1)
- to increase bone mass in men with osteoporosis at high risk for fracture (1.2)
- of glucocorticoid-induced osteoporosis in men and women at high risk for fracture (1.3)
- to increase bone mass in men at high risk for fracture receiving androgen deprivation therapy for nonmetastatic prostate cancer (1.4)
- to increase bone mass in women at high risk for fracture receiving adjuvant aromatase inhibitor therapy for breast cancer (1.5)

2 DOSAGE AND ADMINISTRATION

- Pregnancy must be ruled out prior to administration of Conexxence. (2.1)
- Before initiating Conexxence in patients with advanced chronic kidney disease, including dialysis patients, evaluate for the presence of chronic kidney disease mineral and bone disorder with intact parathyroid hormone, serum calcium, 25(OH) vitamin D, and 1,25(OH)2 vitamin D. (2.2, 5.1, 8.6)
- Conexxence should be administered by a healthcare provider. (2.3)
- Administer 60 mg every 6 months as a subcutaneous injection in the upper arm, upper thigh, or abdomen. (2.3)
- Instruct patients to take calcium 1000 mg daily and at least 400 IU vitamin D daily. (2.3)

3 DOSAGE FORMS AND STRENGTHS

Injection: 60 mg/mL solution in a single-dose prefilled syringe (3)

4 CONTRAINDICATIONS

- Hypocalcemia (4, 5.1)
- Pregnancy (4, 8.1)
- Known hypersensitivity to denosumab products (4, 5.3)

5 WARNINGS AND PRECAUTIONS

- Hypocalcemia: Pre-existing hypocalcemia must be corrected before initiating Conexxence. May worsen, especially in patients with renal impairment. Adequately supplement all patients with calcium and vitamin D. Concomitant use of calcimimetic drugs may also worsen hypocalcemia risk. Evaluate for presence of chronic kidney disease mineral-bone disorder. Monitor serum calcium. (5.1)
- Same Active Ingredient: Patients receiving Conexxence should not receive other denosumab products concomitantly (5.2)
- Hypersensitivity including anaphylactic reactions may occur. Discontinue permanently if a clinically significant reaction occurs. (5.3)
- Osteonecrosis of the jaw: Has been reported with denosumab products. Monitor for symptoms. (5.4)
- Atypical femoral fractures: Have been reported. Evaluate patients with thigh or groin pain to rule out a femoral fracture. (5.5)
- Multiple vertebral fractures have been reported following treatment discontinuation. Patients should be transitioned to another antiresorptive agent if Conexxence is discontinued. (5.6)
- Serious infections including skin infections: May occur, including those leading to hospitalization. Advise patients to seek prompt medical attention if they develop signs or symptoms of infection, including cellulitis. (5.7)
- Dermatologic reactions: Dermatitis, rashes, and eczema have been reported. Consider discontinuing Conexxence if severe symptoms develop. (5.8)
- Severe bone, joint, muscle pain may occur. Discontinue use if severe symptoms develop. (5.9)
- Suppression of bone turnover: Significant suppression has been demonstrated. Monitor for consequences of bone over-suppression. (5.10)

6 ADVERSE REACTIONS

- Postmenopausal osteoporosis: Most common adverse reactions (> 5% and more common than placebo) were: back pain, pain in extremity, hypercholesterolemia, musculoskeletal pain, and cystitis. Pancreatitis has been reported in clinical trials. (6.1)
- Male osteoporosis: Most common adverse reactions (> 5% and more common than placebo) were: back pain, arthralgia, and nasopharyngitis.
- (6.1)
- Glucocorticoid-induced osteoporosis: Most common adverse reactions (> 3% and more common than active-control group) were: back pain, hypertension, bronchitis, and headache. (6.1)
- Bone loss due to hormone ablation for cancer: Most common adverse reactions (≥ 10% and more common than placebo) were: arthralgia and back pain. Pain in extremity and musculoskeletal pain have also been reported in clinical trials. (6.1)

To report SUSPECTED ADVERSE REACTIONS, contact Fresenius Kabi USA, LLC at 1-800-551-7176 or FDA at 1-800-FDA-1088 or www.fda.gov/medwatch.

8 USE IN SPECIFIC POPULATIONS

- Pregnant women and females of reproductive potential: Denosumab products may cause fetal harm when administered to pregnant women. Advise females of reproductive potential to use effective contraception during therapy, and for at least 5 months after the last dose of Conexxence. (8.1, 8.3)
- Pediatric patients: Conexxence is not approved for use in pediatric patients. (8.4)
- Renal impairment: No dose adjustment is necessary in patients with renal impairment. Patients with advanced chronic kidney disease (eGFR < 30 mL/min/1.73 m^2), including dialysis-dependent patients, are at greater risk of severe hypocalcemia. The presence of underlying chronic kidney disease-mineral bone disorder markedly increases the risk of hypocalcemia. (5.1, 8.6)

FULL PRESCRIBING INFORMATION

WARNING: SEVERE HYPOCALCEMIA IN PATIENTS WITH ADVANCED KIDNEY DISEASE

- Patients with advanced chronic kidney disease (eGFR < 30 mL/min/1.73 m^2), including dialysis-dependent patients, are at greater risk of severe hypocalcemia following denosumab products administration. Severe hypocalcemia resulting in hospitalization, life-threatening events and fatal cases have been reported [see Warnings and Precautions (5.1)].
- The presence of chronic kidney disease-mineral bone disorder (CKD-MBD) markedly increases the risk of hypocalcemia in these patients [see Warnings and Precautions (5.1)].
- Prior to initiating Conexxence in patients with advanced chronic kidney disease, evaluate for the presence of CKD-MBD. Treatment with Conexxence in these patients should be supervised by a healthcare provider with expertise in the diagnosis and management of CKD-MBD [see Dosage and Administration (2.2) and Warnings and Precautions (5.1)].

1 INDICATIONS AND USAGE

1.1 Treatment of Postmenopausal Women with Osteoporosis at High Risk for Fracture

Conexxence is indicated for the treatment of postmenopausal women with osteoporosis at high risk for fracture, defined as a history of osteoporotic fracture, or multiple risk factors for fracture; or patients who have failed or are intolerant to other available osteoporosis therapy. In postmenopausal women with osteoporosis, denosumab reduces the incidence of vertebral, nonvertebral, and hip fractures [see Clinical Studies (14.1)].

1.2 Treatment to Increase Bone Mass in Men with Osteoporosis

Conexxence is indicated for treatment to increase bone mass in men with osteoporosis at high risk for fracture, defined as a history of osteoporotic fracture, or multiple risk factors for fracture; or patients who have failed or are intolerant to other available osteoporosis therapy [see Clinical Studies (14.2)].

1.3 Treatment of Glucocorticoid-Induced Osteoporosis

Conexxence is indicated for the treatment of glucocorticoid-induced osteoporosis in men and women at high risk of fracture who are either initiating or continuing systemic glucocorticoids in a daily dosage equivalent to 7.5 mg or greater of prednisone and expected to remain on glucocorticoids for at least 6 months. High risk of fracture is defined as a history of osteoporotic fracture, multiple risk factors for fracture, or patients who have failed or are intolerant to other available osteoporosis therapy [see Clinical Studies (14.3)].

1.4 Treatment of Bone Loss in Men Receiving Androgen Deprivation Therapy for Prostate Cancer

Conexxence is indicated as a treatment to increase bone mass in men at high risk for fracture receiving androgen deprivation therapy (ADT) for nonmetastatic prostate cancer. In these patients denosumab also reduced the incidence of vertebral fractures [see Clinical Studies (14.4)].

1.5 Treatment of Bone Loss in Women Receiving Adjuvant Aromatase Inhibitor Therapy for Breast Cancer

Conexxence is indicated as a treatment to increase bone mass in women at high risk for fracture receiving adjuvant aromatase inhibitor therapy for breast cancer [see Clinical Studies (14.5)].

2 DOSAGE AND ADMINISTRATION

2.1 Pregnancy Testing Prior to Initiation of Conexxence

Pregnancy must be ruled out prior to administration of Conexxence. Perform pregnancy testing in all females of reproductive potential prior to administration of Conexxence. Based on findings in animals, denosumab products can cause fetal harm when administered to pregnant women [see Use in Specific Populations (8.1, 8.3)].

2.2 Laboratory Testing in Patients with Advanced Chronic Kidney Disease Prior to Initiation of Conexxence

In patients with advanced chronic kidney disease [i.e., estimated glomerular filtration rate (eGFR) < 30 mL/min/1.73 m^2], including dialysis-dependent patients, evaluate for the presence of chronic kidney disease mineral and bone disorder (CKD-MBD) with intact parathyroid hormone (iPTH), serum calcium, 25(OH) vitamin D, and 1,25 (OH)2 vitamin D prior to decisions regarding Conexxence treatment. Consider also assessing bone turnover status (serum markers of bone turnover or bone biopsy) to evaluate the underlying bone disease that may be present [see Warnings and Precautions (5.1)].

2.3 Recommended Dosage

Conexxence should be administered by a healthcare provider.

The recommended dose of Conexxence is 60 mg administered as a single subcutaneous injection once every 6 months. Administer Conexxence via subcutaneous injection in the upper arm, the upper thigh, or the abdomen. All patients should receive calcium 1000 mg daily and at least 400 IU vitamin D daily [see Warnings and Precautions (5.1)].

If a dose of Conexxence is missed, administer the injection as soon as the patient is available. Thereafter, schedule injections every 6 months from the date of the last injection.

2.4 Preparation and Administration

Parenteral drug products should be inspected visually for particulate matter and discoloration prior to administration, whenever solution and container permit. Conexxence is a clear, colorless to pale yellow solution that is free from visible particles. Do not use if the solution is discolored or cloudy or if the solution contains particles or foreign particulate matter.

Prior to administration, Conexxence may be removed from the refrigerator and brought to room temperature up to 25°C (77°F) by standing in the original container. This generally takes 15 to 30 minutes. Do not warm Conexxence in any other way [see How Supplied/Storage and Handling (16)]. Do not shake the prefilled syringe.

Instructions for Administration of Conexxence Prefilled Syringe with Needle Safety Guard

IMPORTANT:

In order to minimize accidental needlesticks, the Conexxence single-dose prefilled syringe has an automatic clear needle safety guard.

Conexxence prefilled syringe (Before & After Use). See figure below.

Step 1: Remove Needle Cap (see Figure A)
Do not hold the prefilled syringe by the plunger rod.
Do not twist or bend the needle cap.

Figure A

Step 2: Administer Subcutaneous Injection
Choose an injection site. The recommended injection sites for Conexxence include (see Figure B):

- upper thigh
- abdomen
- upper arm

Figure B

Do not administer into muscle or blood vessel.
Pinch the skin and insert the needle at a 45 to 90-degree
angle. Push the plunger with a slow and constant pressure
until you cannot press further and have injected all the
liquid subcutaneously (see Figure C).
You may hear or feel a “click”.

Figure C

Step 3. Release Plunger
Keeping the prefilled syringe at the injection site, slowly release the plunger and lift syringe off the skin. The clear needle guard will automatically cover the needle (see Figure D).

Do not recap the needle.
Immediately dispose of the used prefilled syringe into a sharps
disposal container.

Figure D

3 DOSAGE FORMS AND STRENGTHS

- Injection: 60 mg/mL clear, colorless to pale yellow solution in a single-dose prefilled syringe.

4 CONTRAINDICATIONS

Conexxence is contraindicated in:

- Patients with hypocalcemia: Pre-existing hypocalcemia must be corrected prior to initiating therapy with Conexxence [see Warnings and Precautions (5.1)].
- Pregnant women: Denosumab products may cause fetal harm when administered to a pregnant woman. In women of reproductive potential, pregnancy testing should be performed prior to initiating treatment with Conexxence [see Use in Specific Populations (8.1)].
- Patients with hypersensitivity to denosumab products: Conexxence is contraindicated in patients with a history of systemic hypersensitivity to any component of the product. Reactions have included anaphylaxis, facial swelling, and urticaria [see Warnings and Precautions (5.3), Adverse Reactions (6.2)].

5 WARNINGS AND PRECAUTIONS

5.1 Severe Hypocalcemia and Mineral Metabolism Changes

Denosumab products can cause severe hypocalcemia and fatal cases have been reported. Pre-existing hypocalcemia must be corrected prior to initiating therapy with Conexxence. Adequately supplement all patients with calcium and vitamin D [see Dosage and Administration (2.1), Contraindications (4), and Adverse Reactions (6.1)].

In patients without advanced chronic kidney disease who are predisposed to hypocalcemia and disturbances of mineral metabolism (e.g. history of hypoparathyroidism, thyroid surgery, parathyroid surgery, malabsorption syndromes, excision of small intestine, treatment with other calcium-lowering drugs), assess serum calcium and mineral levels (phosphorus and magnesium) 10 to14 days after Conexxence injection. In some postmarketing cases, hypocalcemia persisted for weeks or months and required frequent monitoring and intravenous and/or oral calcium replacement, with or without vitamin D.

Patients with Advanced Chronic Kidney Disease

Patients with advanced chronic kidney disease [i.e., eGFR < 30 mL/min/1.73 m^2] including dialysis-dependent patients are at greater risk for severe hypocalcemia following denosumab products administration. Severe hypocalcemia resulting in hospitalization, life-threatening events and fatal cases have been reported. The presence of underlying chronic kidney disease-mineral bone disorder (CKD-MBD, renal osteodystrophy) markedly increases the risk of hypocalcemia. Concomitant use of calcimimetic drugs may also worsen hypocalcemia risk.

To minimize the risk of hypocalcemia in patients with advanced chronic kidney disease, evaluate for the presence of chronic kidney disease mineral and bone disorder with intact parathyroid hormone (iPTH), serum calcium, 25(OH) vitamin D, and 1,25(OH)2 vitamin D prior to decisions regarding Conexxence treatment. Consider also assessing bone turnover status (serum markers of bone turnover or bone biopsy) to evaluate the underlying bone disease that may be present. Monitor serum calcium weekly for the first month after Conexxence administration and monthly thereafter. Instruct all patients with advanced chronic kidney disease, including those who are dialysis-dependent, about the symptoms of hypocalcemia and the importance of maintaining serum calcium levels with adequate calcium and activated vitamin D supplementation. Treatment with Conexxence in these patients should be supervised by a healthcare provider who is experienced in diagnosis and management of CKD-MBD.

5.2 Drug Products with Same Active Ingredient

Patients receiving Conexxence should not receive other denosumab products concomitantly.

5.3 Hypersensitivity

Clinically significant hypersensitivity including anaphylaxis has been reported with denosumab products. Symptoms have included hypotension, dyspnea, throat tightness, facial and upper airway edema, pruritus, and urticaria. If an anaphylactic or other clinically significant allergic reaction occurs, initiate appropriate therapy and discontinue further use of Conexxence [see Contraindications (4), Adverse Reactions (6.2)].

5.4 Osteonecrosis of the Jaw

Osteonecrosis of the jaw (ONJ), which can occur spontaneously, is generally associated with tooth extraction and/or local infection with delayed healing. ONJ has been reported in patients receiving denosumab products [see Adverse Reactions (6.1)]. A routine oral exam should be performed by the prescriber prior to initiation of Conexxence treatment. A dental examination with appropriate preventive dentistry is recommended prior to treatment with Conexxence in patients with risk factors for ONJ such as invasive dental procedures (e.g. tooth extraction, dental implants, oral surgery), diagnosis of cancer, concomitant therapies (e.g. chemotherapy, corticosteroids, angiogenesis inhibitors), poor oral hygiene, and comorbid disorders (e.g. periodontal and/or other pre-existing dental disease, anemia, coagulopathy, infection, ill-fitting dentures). Good oral hygiene practices should be maintained during treatment with Conexxence. Concomitant administration of drugs associated with ONJ may increase the risk of developing ONJ. The risk of ONJ may increase with duration of exposure to denosumab products.

For patients requiring invasive dental procedures, clinical judgment of the treating physician and/or oral surgeon should guide the management plan of each patient based on individual benefit-risk assessment.

Patients who are suspected of having or who develop ONJ while on Conexxence should receive care by a dentist or an oral surgeon. In these patients, extensive dental surgery to treat ONJ may exacerbate the condition. Discontinuation of Conexxence therapy should be considered based on individual benefit-risk assessment.

5.5 Atypical Subtrochanteric and Diaphyseal Femoral Fractures

Atypical low energy or low trauma fractures of the shaft have been reported in patients receiving denosumab products [see Adverse Reactions (6.1)]. These fractures can occur anywhere in the femoral shaft from just below the lesser trochanter to above the supracondylar flare and are transverse or short oblique in orientation without evidence of comminution. Causality has not been established as these fractures also occur in osteoporotic patients who have not been treated with antiresorptive agents.

Atypical femoral fractures most commonly occur with minimal or no trauma to the affected area. They may be bilateral, and many patients report prodromal pain in the affected area, usually presenting as dull, aching thigh pain, weeks to months before a complete fracture occurs. A number of reports note that patients were also receiving treatment with glucocorticoids (e.g. prednisone) at the time of fracture.

During Conexxence treatment, patients should be advised to report new or unusual thigh, hip, or groin pain. Any patient who presents with thigh or groin pain should be suspected of having an atypical fracture and should be evaluated to rule out an incomplete femur fracture. Patients presenting with an atypical femur fracture should also be assessed for symptoms and signs of fracture in the contralateral limb. Interruption of Conexxence therapy should be considered, pending a benefit-risk assessment, on an individual basis.

5.6 Multiple Vertebral Fractures (MVF) Following Discontinuation of Treatment

Following discontinuation of denosumab treatment, fracture risk increases, including the risk of multiple vertebral fractures. Treatment with denosumab results in significant suppression of bone turnover and cessation of denosumab treatment results in increased bone turnover above pretreatment values 9 months after the last dose of denosumab. Bone turnover then returns to pretreatment values 24 months after the last dose of denosumab. In addition, bone mineral density (BMD) returns to pretreatment values within 18 months after the last injection [see Clinical Pharmacology (12.2), Clinical Studies (14.1)].

New vertebral fractures occurred as early as 7 months (on average 19 months) after the last dose of denosumab. Prior vertebral fracture was a predictor of multiple vertebral fractures after denosumab discontinuation. Evaluate an individual's benefit-risk before initiating treatment with Conexxence.

If Conexxence treatment is discontinued, patients should be transitioned to an alternative antiresorptive therapy [see Adverse Reactions (6.1)].

5.7 Serious Infections

In a clinical trial of over 7800 women with postmenopausal osteoporosis, serious infections leading to hospitalization were reported more frequently in the denosumab group than in the placebo group [see Adverse Reactions (6.1)]. Serious skin infections, as well as infections of the abdomen, urinary tract, and ear, were more frequent in patients treated with denosumab. Endocarditis was also reported more frequently in denosumab-treated patients. The incidence of opportunistic infections was similar between placebo and denosumab groups, and the overall incidence of infections was similar between the treatment groups. Advise patients to seek prompt medical attention if they develop signs or symptoms of severe infection, including cellulitis.

Patients on concomitant immunosuppressant agents or with impaired immune systems may be at increased risk for serious infections. Consider the benefit-risk profile in such patients before treating with Conexxence. In patients who develop serious infections while on Conexxence, prescribers should assess the need for continued Conexxence therapy.

5.8 Dermatologic Adverse Reactions

In a large clinical trial of over 7800 women with postmenopausal osteoporosis, epidermal and dermal adverse events such as dermatitis, eczema, and rashes occurred at a significantly higher rate in the denosumab group compared to the placebo group. Most of these events were not specific to the injection site [see Adverse Reactions (6.1)]. Consider discontinuing Conexxence if severe symptoms develop.

5.9 Musculoskeletal Pain

In postmarketing experience, severe and occasionally incapacitating bone, joint, and/or muscle pain has been reported in patients taking denosumab products [see Adverse Reactions (6.2)]. The time to onset of symptoms varied from one day to several months after starting denosumab products. Consider discontinuing use if severe symptoms develop [see Patient Counseling Information (17)].

5.10 Suppression of Bone Turnover

In clinical trials in women with postmenopausal osteoporosis, treatment with denosumab resulted in significant suppression of bone remodeling as evidenced by markers of bone turnover and bone histomorphometry [see Clinical Pharmacology (12.2), Clinical Studies (14.1)]. The significance of these findings and the effect of long-term treatment with denosumab products are unknown. The long-term consequences of the degree of suppression of bone remodeling observed with denosumab may contribute to adverse outcomes such as osteonecrosis of the jaw, atypical fractures, and delayed fracture healing. Monitor patients for these consequences.

5.11 Hypercalcemia in Pediatric Patients with Osteogenesis Imperfecta

Conexxence is not approved for use in pediatric patients. Hypercalcemia has been reported in pediatric patients with osteogenesis imperfecta treated with denosumab products. Some cases required hospitalization [see Use in Specific Populations (8.4)].

6 ADVERSE REACTIONS

The following serious adverse reactions are discussed below and also elsewhere in the labeling:

- Severe Hypocalcemia and Mineral Metabolism Changes [see Warnings and Precautions (5.1)]
- Hypersensitivity [see Warnings and Precautions (5.3)]
- Osteonecrosis of the Jaw [see Warnings and Precautions (5.4)]
- Atypical Subtrochanteric and Diaphyseal Femoral Fractures [see Warnings and Precautions (5.5)]
- Multiple Vertebral Fractures (MVF) Following Treatment Discontinuation of Treatment [see Warnings and Precautions (5.6)]
- Serious Infections [see Warnings and Precautions (5.7)]
- Dermatologic Adverse Reactions [see Warnings and Precautions (5.8)]

The most common adverse reactions reported with denosumab products in patients with postmenopausal osteoporosis are back pain, pain in extremity, musculoskeletal pain, hypercholesterolemia, and cystitis.

The most common adverse reactions reported with denosumab products in men with osteoporosis are back pain, arthralgia, and nasopharyngitis.

The most common adverse reactions reported with denosumab products in patients with glucocorticoid-induced osteoporosis are back pain, hypertension, bronchitis, and headache.

The most common (per patient incidence ≥ 10%) adverse reactions reported with denosumab products in patients with bone loss receiving androgen deprivation therapy for prostate cancer or adjuvant aromatase inhibitor therapy for breast cancer are arthralgia and back pain. Pain in extremity and musculoskeletal pain have also been reported in clinical trials.

The most common adverse reactions leading to discontinuation of denosumab products in patients with postmenopausal osteoporosis are back pain and constipation.

6.1 Clinical Trials Experience

Because clinical studies are conducted under widely varying conditions, adverse reaction rates observed in the clinical studies of a drug cannot be directly compared to rates in the clinical studies of another drug and may not reflect the rates observed in clinical practice.

Treatment of Postmenopausal Women with Osteoporosis

The safety of denosumab in the treatment of postmenopausal osteoporosis was assessed in a 3-year, randomized, double-blind, placebo-controlled, multinational study of 7808 postmenopausal women aged 60 to 91 years. A total of 3876 women were exposed to placebo and 3886 women were exposed to denosumab administered subcutaneously once every 6 months as a single 60 mg dose. All women were instructed to take at least 1000 mg of calcium and 400 IU of vitamin D supplementation per day.

The incidence of all-cause mortality was 2.3% (n = 90) in the placebo group and 1.8% (n = 70) in the denosumab group. The incidence of nonfatal serious adverse events was 24.2% in the placebo group and 25.0% in the denosumab group. The percentage of patients who withdrew from the study due to adverse events was 2.1% and 2.4% for the placebo and denosumab groups, respectively. The most common adverse reactions reported with denosumab in patients with postmenopausal osteoporosis are back pain, pain in extremity, musculoskeletal pain, hypercholesterolemia, and cystitis.

Adverse reactions reported in ≥ 2% of postmenopausal women with osteoporosis and more frequently in the denosumab-treated women than in the placebo-treated women are shown in the table below.

Table 1. Adverse Reactions Occurring in ≥ 2% of Patients with Osteoporosis and More Frequently than in Placebo-treated Patients
Preferred Term | Denosumab (N = 3886) n (%) | Placebo (N = 3876) n (%)
Back pain Pain in extremity Musculoskeletal pain Hypercholesterolemia Cystitis Vertigo Upper respiratory tract infection Edema peripheral Sciatica Bone pain Abdominal pain upper Anemia Insomnia Myalgia Angina pectoris Rash Pharyngitis Asthenia Pruritus Flatulence Spinal osteoarthritis Gastroesophageal reflux disease Herpes zoster | 1347 (34.7) 453 (11.7) 297 (7.6) 280 (7.2) 228 (5.9) 195 (5.0) 190 (4.9) 189 (4.9) 178 (4.6) 142 (3.7) 129 (3.3) 129 (3.3) 126 (3.2) 114 (2.9) 101 (2.6) 96 (2.5) 91 (2.3) 90 (2.3) 87 (2.2) 84 (2.2) 82 (2.1) 80 (2.1) 79 (2.0) | 1340 (34.6) 430 (11.1) 291 (7.5) 236 (6.1) 225 (5.8) 187 (4.8) 167 (4.3) 155 (4.0) 149 (3.8) 117 (3.0) 111 (2.9) 107 (2.8) 122 (3.1) 94 (2.4) 87 (2.2) 79 (2.0) 78 (2.0) 73 (1.9) 82 (2.1) 53 (1.4) 64 (1.7) 66 (1.7) 72 (1.9)

Hypocalcemia

Decreases in serum calcium levels to less than 8.5 mg/dL at any visit were reported in 0.4% women in the placebo group and 1.7% women in the denosumab group. The nadir in serum calcium level occurred at approximately day 10 after denosumab dosing in subjects with normal renal function.

In clinical studies, subjects with impaired renal function were more likely to have greater reductions in serum calcium levels compared to subjects with normal renal function. In a study of 55 subjects with varying degrees of renal function, serum calcium levels < 7.5 mg/dL or symptomatic hypocalcemia were observed in 5 subjects. These included no subjects in the normal renal function group, 10% of subjects in the creatinine clearance 50 to 80 mL/min group, 29% of subjects in the creatinine clearance < 30 mL/min group, and 29% of subjects in the hemodialysis group. These subjects did not receive calcium and vitamin D supplementation. In a study of 4550 postmenopausal women with osteoporosis, the mean change from baseline in serum calcium level 10 days after denosumab dosing was -5.5% in subjects with creatinine clearance < 30 mL/min vs. -3.1% in subjects with creatinine clearance ≥ 30 mL/min.

Serious Infections

Receptor activator of nuclear factor kappa-B ligand (RANKL) is expressed on activated T and B lymphocytes and in lymph nodes. Therefore, a RANKL inhibitor such as denosumab products may increase the risk of infection.

In the clinical study of 7808 postmenopausal women with osteoporosis, the incidence of infections resulting in death was 0.2% in both placebo and denosumab treatment groups. However, the incidence of nonfatal serious infections was 3.3% in the placebo and 4.0% in the denosumab groups. Hospitalizations due to serious infections in the abdomen (0.7% placebo vs. 0.9% denosumab), urinary tract (0.5% placebo vs. 0.7% denosumab), and ear (0.0% placebo vs. 0.1% denosumab) were reported. Endocarditis was reported in no placebo patients and 3 patients receiving denosumab.

Skin infections, including erysipelas and cellulitis, leading to hospitalization were reported more frequently in patients treated with denosumab (< 0.1% placebo vs. 0.4% denosumab).

The incidence of opportunistic infections was similar to that reported with placebo.

Dermatologic Adverse Reactions

A significantly higher number of patients treated with denosumab developed epidermal and dermal adverse events (such as dermatitis, eczema, and rashes), with these events reported in 8.2% of the placebo and 10.8% of the denosumab groups (p < 0.0001). Most of these events were not specific to the injection site [see Warnings and Precautions (5.8)].

Osteonecrosis of the Jaw

ONJ has been reported in the osteoporosis clinical trial program in patients treated with denosumab [see Warnings and Precautions (5.4)].

Atypical Subtrochanteric and Diaphyseal Femoral Fractures

In the osteoporosis clinical trial program, atypical femoral fractures were reported in patients treated with denosumab. The duration of denosumab exposure to time of atypical femoral fracture diagnosis was as early as 2½ years [see Warnings and Precautions (5.5)].

Multiple Vertebral Fractures (MVF) Following Treatment Discontinuation

In the osteoporosis clinical trial program, multiple vertebral fractures were reported in patients after discontinuation of denosumab. In the phase 3 trial in women with postmenopausal osteoporosis, 6% of women who discontinued denosumab and remained in the study developed new vertebral fractures, and 3% of women who discontinued denosumab and remained in the study developed multiple new vertebral fractures. The mean time to onset of multiple vertebral fractures was 17 months (range: 7-43 months) after the last injection of denosumab. Prior vertebral fracture was a predictor of multiple vertebral fractures after discontinuation [see Warnings and Precautions (5.6)].

Pancreatitis

Pancreatitis was reported in 4 patients (0.1%) in the placebo and 8 patients (0.2%) in the denosumab groups. Of these reports, 1 patient in the placebo group and all 8 patients in the denosumab group had serious events, including one death in the denosumab group. Several patients had a prior history of pancreatitis. The time from product administration to event occurrence was variable.

New Malignancies

The overall incidence of new malignancies was 4.3% in the placebo and 4.8% in the denosumab groups. New malignancies related to the breast (0.7% placebo vs. 0.9% denosumab), reproductive system (0.2% placebo vs. 0.5% denosumab), and gastrointestinal system (0.6% placebo vs. 0.9% denosumab) were reported. A causal relationship to drug exposure has not been established.

Treatment to Increase Bone Mass in Men with Osteoporosis

The safety of denosumab in the treatment of men with osteoporosis was assessed in a 1-year randomized, double-blind, placebo-controlled study. A total of 120 men were exposed to placebo and 120 men were exposed to denosumab administered subcutaneously once every 6 months as a single 60 mg dose. All men were instructed to take at least 1000 mg of calcium and 800 IU of vitamin D supplementation per day.

The incidence of all-cause mortality was 0.8% (n = 1) in the placebo group and 0.8% (n = 1) in the denosumab group. The incidence of nonfatal serious adverse events was 7.5% in the placebo group and 8.3% in the denosumab group. The percentage of patients who withdrew from the study due to adverse events was 0% and 2.5% for the placebo and denosumab groups, respectively.

Adverse reactions reported in ≥ 5% of men with osteoporosis and more frequently with denosumab than in the placebo-treated patients were: back pain (6.7% placebo vs. 8.3% denosumab), arthralgia (5.8% placebo vs. 6.7% denosumab), and nasopharyngitis (5.8% placebo vs. 6.7% denosumab).

Serious Infections

Serious infection was reported in 1 patient (0.8%) in the placebo group and no patients in the denosumab group.

Dermatologic Adverse Reactions

Epidermal and dermal adverse events (such as dermatitis, eczema, and rashes) were reported in 4 patients (3.3%) in the placebo group and 5 patients (4.2%) in the denosumab group.

Osteonecrosis of the Jaw

No cases of ONJ were reported.

Pancreatitis

Pancreatitis was reported in 1 patient (0.8%) in the placebo group and 1 patient (0.8%) in the denosumab group.

New Malignancies

New malignancies were reported in no patients in the placebo group and 4 (3.3%) patients (3 prostate cancers, 1 basal cell carcinoma) in the denosumab group.

Treatment of Glucocorticoid-Induced Osteoporosis

The safety of denosumab in the treatment of glucocorticoid-induced osteoporosis was assessed in the 1-year, primary analysis of a 2-year randomized, multicenter, double-blind, parallel-group, active-controlled study of 795 patients (30% men and 70% women) aged 20 to 94 (mean age of 63 years) treated with greater than or equal to 7.5 mg/day oral prednisone (or equivalent). A total of 384 patients were exposed to 5 mg oral daily bisphosphonate (active-control) and 394 patients were exposed to denosumab administered once every 6 months as a 60 mg subcutaneous dose. All patients were instructed to take at least 1000 mg of calcium and 800 IU of vitamin D supplementation per day.

The incidence of all-cause mortality was 0.5% (n = 2) in the active-control group and 1.5% (n = 6) in the denosumab group. The incidence of serious adverse events was 17% in the active-control group and 16% in the denosumab group. The percentage of patients who withdrew from the study due to adverse events was 3.6% and 3.8% for the active-control and denosumab groups, respectively.

Adverse reactions reported in ≥ 2% of patients with glucocorticoid-induced osteoporosis and more frequently with denosumab than in the active-control-treated patients are shown in the table below.

Table 2. Adverse Reactions Occurring in ≥ 2% of Patients with Glucocorticoid-induced Osteoporosis and More Frequently with Denosumab than in Active-Control-treated Patients
Preferred Term | Denosumab (N=394) n (%) | Oral Daily Bisphosphonate (Active-Control) (N=384) n (%)
Back pain | 18 (4.6) | 17 (4.4)
Hypertension | 15 (3.8) | 13 (3.4)
Bronchitis | 15 (3.8) | 11 (2.9)
Headache | 14 (3.6) | 7 (1.8)
Dyspepsia | 12 (3.0) | 10 (2.6)
Urinary tract infection | 12 (3.0) | 8 (2.1)
Abdominal pain upper | 12 (3.0) | 7 (1.8)
Upper respiratory tract infection | 11 (2.8) | 10 (2.6)
Constipation | 11 (2.8) | 6 (1.6)
Vomiting | 10 (2.5) | 6 (1.6)
Dizziness | 9 (2.3) | 8 (2.1)
Fall | 8 (2.0) | 7 (1.8)
Polymyalgia rheumatica* | 8 (2.0) | 1 (0.3)
*Events of worsening of underlying polymyalgia rheumatica.

Osteonecrosis of the Jaw

No cases of ONJ were reported.

Atypical Subtrochanteric and Diaphyseal Femoral Fractures

Atypical femoral fractures were reported in 1 patient treated with denosumab. The duration of denosumab exposure to time of atypical femoral fracture diagnosis was at 8.0 months [see Warnings and Precautions (5.5)].

Serious Infections

Serious infection was reported in 15 patients (3.9%) in the active-control group and 17 patients (4.3%) in the denosumab group.

Dermatologic Adverse Reactions

Epidermal and dermal adverse events (such as dermatitis, eczema, and rashes) were reported in 16 patients (4.2%) in the active-control group and 15 patients (3.8%) in the denosumab group.

Treatment of Bone Loss in Patients Receiving Androgen Deprivation Therapy for Prostate Cancer or Adjuvant Aromatase Inhibitor Therapy for Breast Cancer

The safety of denosumab in the treatment of bone loss in men with nonmetastatic prostate cancer receiving androgen deprivation therapy (ADT) was assessed in a 3-year, randomized, double-blind, placebo-controlled, multinational study of 1468 men aged 48 to 97 years. A total of 725 men were exposed to placebo and 731 men were exposed to denosumab administered once every 6 months as a single 60 mg subcutaneous dose. All men were instructed to take at least 1000 mg of calcium and 400 IU of vitamin D supplementation per day.

The incidence of serious adverse events was 30.6% in the placebo group and 34.6% in the denosumab group. The percentage of patients who withdrew from the study due to adverse events was 6.1% and 7.0% for the placebo and denosumab groups, respectively.

The safety of denosumab in the treatment of bone loss in women with nonmetastatic breast cancer receiving aromatase inhibitor (AI) therapy was assessed in a 2-year, randomized, double-blind, placebo-controlled, multinational study of 252 postmenopausal women aged 35 to 84 years. A total of 120 women were exposed to placebo and 129 women were exposed to denosumab administered once every 6 months as a single 60 mg subcutaneous dose. All women were instructed to take at least 1000 mg of calcium and 400 IU of vitamin D supplementation per day.

The incidence of serious adverse events was 9.2% in the placebo group and 14.7% in the denosumab group. The percentage of patients who withdrew from the study due to adverse events was 4.2% and 0.8% for the placebo and denosumab groups, respectively.

Adverse reactions reported in ≥ 10% of denosumab -treated patients receiving ADT for prostate cancer or adjuvant AI therapy for breast cancer, and more frequently than in the placebo-treated patients were: arthralgia (13.0% placebo vs. 14.3% denosumab) and back pain (10.5% placebo vs. 11.5% denosumab). Pain in extremity (7.7% placebo vs. 9.9% denosumab) and musculoskeletal pain (3.8% placebo vs. 6.0% denosumab) have also been reported in clinical trials. Additionally, in denosumab-treated men with nonmetastatic prostate cancer receiving ADT, a greater incidence of cataracts was observed (1.2% placebo vs. 4.7% denosumab). Hypocalcemia (serum calcium < 8.4 mg/dL) was reported only in denosumab -treated patients (2.4% vs. 0.0%) at the month 1 visit.

6.2 Postmarketing Experience

Because postmarketing reactions are reported voluntarily from a population of uncertain size, it is not always possible to reliably estimate their frequency or establish a causal relationship to drug exposure.

The following adverse reactions have been identified during post approval use of denosumab products:

- Drug-related hypersensitivity reactions: anaphylaxis, rash, urticaria, facial swelling, and erythema
- Hypocalcemia: severe symptomatic hypocalcemia resulting in hospitalization, life-threatening events, and fatal cases
- Musculoskeletal pain, including severe cases
- Parathyroid hormone (PTH): Marked elevation in serum PTH in patients with severe renal impairment (creatinine clearance < 30 mL/min) or receiving dialysis
- Multiple vertebral fractures following treatment discontinuation
- Cutaneous and mucosal lichenoid drug eruptions (e.g. lichen planus-like reactions)
- Alopecia
- Vasculitis (e.g. ANCA positive vasculitis, leukocytoclastic vasculitis)
- Drug reaction with eosinophilia and systemic symptoms (DRESS) syndrome

8 USE IN SPECIFIC POPULATIONS

8.1 Pregnancy

Risk Summary

Conexxence is contraindicated for use in pregnant women because it may cause harm to a fetus. There are insufficient data with denosumab products use in pregnant women to inform any drug-associated risks for adverse developmental outcomes. In utero denosumab exposure from cynomolgus monkeys dosed monthly with denosumab throughout pregnancy at a dose 50-fold higher than the recommended human dose based on body weight resulted in increased fetal loss, stillbirths, and postnatal mortality, and absent lymph nodes, abnormal bone growth, and decreased neonatal growth [see Data].

Data

Animal Data

The effects of denosumab on prenatal development have been studied in both cynomolgus monkeys and genetically engineered mice in which RANK ligand (RANKL) expression was turned off by gene removal (a “knockout mouse”). In cynomolgus monkeys dosed subcutaneously with denosumab throughout pregnancy starting at gestational day 20 and at a pharmacologically active dose 50-fold higher than the recommended human dose based on body weight, there was increased fetal loss during gestation, stillbirths, and postnatal mortality. Other findings in offspring included absence of axillary, inguinal, mandibular, and mesenteric lymph nodes; abnormal bone growth, reduced bone strength, reduced hematopoiesis, dental dysplasia, and tooth malalignment; and decreased neonatal growth. At birth out to 1 month of age, infants had measurable blood levels of denosumab (22-621% of maternal levels).

Following a recovery period from birth out to 6 months of age, the effects on bone quality and strength returned to normal; there were no adverse effects on tooth eruption, though dental dysplasia was still apparent; axillary and inguinal lymph nodes remained absent, while mandibular and mesenteric lymph nodes were present, though small; and minimal to moderate mineralization in multiple tissues was seen in one recovery animal. There was no evidence of maternal harm prior to labor; adverse maternal effects occurred infrequently during labor. Maternal mammary gland development was normal. There was no fetal NOAEL (no observable adverse effect level) established for this study because only one dose of 50 mg/kg was evaluated. Mammary gland histopathology at 6 months of age was normal in female offspring exposed to denosumab in utero; however, development and lactation have not been fully evaluated.

In RANKL knockout mice, absence of RANKL (the target of denosumab) also caused fetal lymph node agenesis and led to postnatal impairment of dentition and bone growth. Pregnant RANKL knockout mice showed altered maturation of the maternal mammary gland, leading to impaired lactation [see Use in Specific Populations (8.2), Nonclinical Toxicology (13.2)].

The no effect dose for denosumab product-induced teratogenicity is unknown. However, a Cmax of 22.9 ng/mL was identified in cynomolgus monkeys as a level in which no biologic effects (NOEL) of denosumab were observed (no inhibition of RANKL) [see Clinical Pharmacology (12.3)].

8.2 Lactation

Risk Summary

There is no information regarding the presence of denosumab products in human milk, the effects on the breastfed infant, or the effects on milk production. Denosumab was detected in the maternal milk of cynomolgus monkeys up to 1 month after the last dose of denosumab (≤ 0.5% milk:serum ratio) and maternal mammary gland development was normal, with no impaired lactation. However, pregnant RANKL knockout mice showed altered maturation of the maternal mammary gland, leading to impaired lactation [see Use in Specific Populations (8.1), Nonclinical Toxicology (13.2)].

8.3 Females and Males of Reproductive Potential

Based on findings in animals, denosumab products can cause fetal harm when administered to a pregnant woman [see Use in Specific Populations (8.1)].

Pregnancy Testing

Verify the pregnancy status of females of reproductive potential prior to initiating Conexxence treatment.

Contraception

Females

Advise females of reproductive potential to use effective contraception during therapy, and for at least 5 months after the last dose of Conexxence.

Males

Denosumab was present at low concentrations (approximately 2% of serum exposure) in the seminal fluid of male subjects given denosumab. Following vaginal intercourse, the maximum amount of denosumab delivered to a female partner would result in exposures approximately 11,000 times lower than the prescribed 60 mg subcutaneous dose, and at least 38 times lower than the NOEL in monkeys.

Therefore, male condom use would not be necessary as it is unlikely that a female partner or fetus would be exposed to pharmacologically relevant concentrations of denosumab products via seminal fluid [see Clinical Pharmacology (12.3)].

8.4 Pediatric Use

The safety and effectiveness of Conexxence have not been established in pediatric patients.

In one multicenter, open-label study with denosumab conducted in 153 pediatric patients with osteogenesis imperfecta, aged 2 to 17 years, evaluating fracture risk reduction, efficacy was not demonstrated.

Hypercalcemia has been reported in pediatric patients with osteogenesis imperfecta treated with denosumab products. Some cases required hospitalization and were complicated by acute renal injury [see Warnings and Precautions (5.11)]. Clinical studies in pediatric patients with osteogenesis imperfecta were terminated early due to the occurrence of life-threatening events and hospitalizations due to hypercalcemia.

Based on results from animal studies, denosumab may negatively affect long-bone growth and dentition in pediatric patients below the age of 4 years.

Juvenile Animal Toxicity Data

Treatment with denosumab products may impair long-bone growth in children with open growth plates and may inhibit eruption of dentition. In neonatal rats, inhibition of RANKL (the target of denosumab therapy) with a construct of osteoprotegerin bound to Fc (OPG-Fc) at doses ≤ 10 mg/kg was associated with inhibition of bone growth and tooth eruption. Adolescent primates treated with denosumab at doses 10 and 50 times (10 and 50 mg/kg dose) higher than the recommended human dose of 60 mg administered every 6 months, based on body weight (mg/kg), had abnormal growth plates, considered to be consistent with the pharmacological activity of denosumab [see Nonclinical Toxicology (13.2)].

Cynomolgus monkeys exposed in utero to denosumab exhibited bone abnormalities, an absence of axillary, inguinal, mandibular, and mesenteric lymph nodes, reduced hematopoiesis, tooth malalignment, and decreased neonatal growth. Some bone abnormalities recovered once exposure was ceased following birth; however, axillary and inguinal lymph nodes remained absent 6 months post-birth [see Use in Specific Populations (8.1)].

8.5 Geriatric Use

Of the total number of patients in clinical studies of denosumab, 9943 patients (76%) were ≥ 65 years old, while 3576 (27%) were ≥ 75 years old. Of the patients in the osteoporosis study in men, 133 patients (55%) were ≥ 65 years old, while 39 patients (16%) were ≥ 75 years old. Of the patients in the glucocorticoid-induced osteoporosis study, 355 patients (47%) were ≥ 65 years old, while 132 patients (17%) were ≥ 75 years old. No overall differences in safety or efficacy were observed between these patients and younger patients, and other reported clinical experience has not identified differences in responses between the elderly and younger patients, but greater sensitivity of some older individuals cannot be ruled out.

8.6 Renal Impairment

No dose adjustment is necessary in patients with renal impairment.

Severe hypocalcemia resulting in hospitalization, life-threatening events and fatal cases have been reported postmarketing. In clinical studies, patients with advanced chronic kidney disease (i.e., eGFR < 30 mL/min/1.73 m^2), including dialysis-dependent patients, were at greater risk of developing hypocalcemia. The presence of underlying chronic kidney disease-mineral bone disorder (CKD-MBD, renal osteodystrophy) markedly increases the risk of hypocalcemia. Concomitant use of calcimimetic drugs may also worsen hypocalcemia risk. Consider the benefits and risks to the patient when administering Conexxence to patients with advanced chronic kidney disease. Monitor calcium and mineral levels (phosphorus and magnesium). Adequate intake of calcium and vitamin D is important in patients with advanced chronic kidney disease including dialysis-dependent patients [see Dosage and Administration (2.2), Warnings and Precautions (5.1), Adverse Reactions (6.1) and Clinical Pharmacology (12.3)].

11 DESCRIPTION

Denosumab-bnht is a human IgG2 monoclonal antibody with affinity and specificity for human RANKL (receptor activator of nuclear factor kappa-B ligand). Denosumab-bnht has an approximate molecular weight of 147 kDa and is produced in genetically engineered mammalian (Chinese hamster ovary) cells.

Conexxence (denosumab-bnht) injection is a sterile, preservative-free, clear, colorless to pale yellow solution for subcutaneous use.

Each 1 mL single-dose prefilled syringe of Conexxence contains 60 mg denosumab-bnht (60 mg/mL solution), 0.23 mg glacial acetic acid, 0.1 mg polysorbate 20, 1.07 mg sodium acetate, 47 mg sorbitol, and Water for Injection (USP). The pH is 5.2.

12 CLINICAL PHARMACOLOGY

12.1 Mechanism of Action

Denosumab products bind to RANKL, a transmembrane or soluble protein essential for the formation, function, and survival of osteoclasts, the cells responsible for bone resorption. Denosumab products prevent RANKL from activating its receptor, RANK, on the surface of osteoclasts and their precursors. Prevention of the RANKL/RANK interaction inhibits osteoclast formation, function, and survival, thereby decreasing bone resorption and increasing bone mass and strength in both cortical and trabecular bone.

12.2 Pharmacodynamics

In clinical studies, treatment with 60 mg of denosumab resulted in reduction in the bone resorption marker serum type 1 C-telopeptide (CTX) by approximately 85% by 3 days, with maximal reductions occurring by 1 month. CTX levels were below the limit of assay quantitation (0.049 ng/mL) in 39% to 68% of patients 1 to 3 months after dosing of denosumab. At the end of each dosing interval, CTX reductions were partially attenuated from a maximal reduction of ≥ 87% to ≥ 45% (range: 45% to 80%), as serum denosumab levels diminished, reflecting the reversibility of the effects of denosumab on bone remodeling. These effects were sustained with continued treatment. Upon reinitiation, the degree of inhibition of CTX by denosumab was similar to that observed in patients initiating denosumab treatment.

Consistent with the physiological coupling of bone formation and resorption in skeletal remodeling, subsequent reductions in bone formation markers (i.e., osteocalcin and procollagen type 1 N-terminal peptide [P1NP]) were observed starting 1 month after the first dose of denosumab. After discontinuation of denosumab therapy, markers of bone resorption increased to levels 40% to 60% above pretreatment values but returned to baseline levels within 12 months.

12.3 Pharmacokinetics

In a study conducted in healthy male and female volunteers (n = 73, age range: 18 to 64 years) following a single subcutaneously administered denosumab dose of 60 mg, the mean area-under-the-concentration-time curve up to 16 weeks (AUC0-16 weeks) of denosumab was 316 mcg⋅day/mL (standard deviation [SD] = 101 mcg⋅day/mL). The mean maximum denosumab concentration (Cmax) was 6.75 mcg/mL (SD = 1.89 mcg/mL). No accumulation or change in denosumab pharmacokinetics with time is observed with multiple dosing of 60 mg subcutaneously administered once every 6 months.

Absorption

Following subcutaneous administration, the median time to maximum denosumab concentration (Tmax) was 10 days (range: 3 to 21 days).

Distribution

The mean volume of distribution for denosumab was 5.2 L (SD = 1.7 L).

Elimination

Serum denosumab concentrations declined over a period of 4 to 5 months with a mean half-life of 25.4 days (SD = 8.5 days; n = 46).

A population pharmacokinetic analysis was performed to evaluate the effects of demographic characteristics. This analysis showed no notable differences in pharmacokinetics with age (in postmenopausal women), race, or body weight (36 to 140 kg).

Seminal Fluid Pharmacokinetic Study

Serum and seminal fluid concentrations of denosumab were measured in 12 healthy male volunteers (age range: 43-65 years). After a single 60 mg subcutaneous administration of denosumab, the mean (± SD) Cmax values in the serum and seminal fluid samples were 6170 (± 2070) and 100 (± 81.9) ng/mL, respectively, resulting in a maximum seminal fluid concentration of approximately 2% of serum levels. The median (range) Tmax values in the serum and seminal fluid samples were 8.0 (7.9 to 21) and 21 (8.0 to 49) days, respectively. Among the subjects, the highest denosumab concentration in seminal fluid was 301 ng/mL at 22 days post-dose. On the first day of measurement (10 days post-dose), nine of eleven subjects had quantifiable concentrations in semen. On the last day of measurement (106 days post-dose), five subjects still had quantifiable concentrations of denosumab in seminal fluid, with a mean (± SD) seminal fluid concentration of 21.1 (± 36.5) ng/mL across all subjects (n = 12).

Drug Interactions

In a study of 19 postmenopausal women with low BMD and rheumatoid arthritis treated with etanercept (50 mg subcutaneous injection once weekly), a single-dose of denosumab (60 mg subcutaneous injection) was administered 7 days after the previous dose of etanercept. No clinically significant changes in the pharmacokinetics of etanercept were observed.

Cytochrome P450 substrates

In a study of 17 postmenopausal women with osteoporosis, midazolam (2 mg oral) was administered 2 weeks after a single-dose of denosumab (60 mg subcutaneous injection), which approximates the Tmax of denosumab. Denosumab did not affect the pharmacokinetics of midazolam, which is metabolized by cytochrome P450 3A4 (CYP3A4). This indicates that denosumab products should not alter the pharmacokinetics of drugs metabolized by CYP3A4 in postmenopausal women with osteoporosis.

Specific Populations

Gender: Mean serum denosumab concentration-time profiles observed in a study conducted in healthy men ≥ 50 years were similar to those observed in a study conducted in postmenopausal women using the same dose regimen.

Age: The pharmacokinetics of denosumab were not affected by age across all populations studied whose ages ranged from 28 to 87 years.

Race: The pharmacokinetics of denosumab were not affected by race.

Renal Impairment: In a study of 55 patients with varying degrees of renal function, including patients on dialysis, the degree of renal impairment had no effect on the pharmacokinetics of denosumab; thus, dose adjustment for renal impairment is not necessary.

Hepatic Impairment: No clinical studies have been conducted to evaluate the effect of hepatic impairment on the pharmacokinetics of denosumab products.

12.6 Immunogenicity

The observed incidence of anti-drug antibodies is highly dependent on the sensitivity and specificity of the assay. Differences in assay methods preclude meaningful comparisons of the incidence of anti-drug antibodies in the studies described below with the incidence of anti-drug antibodies in other studies, including those of denosumab or of other denosumab products.

Using an electrochemiluminescent bridging immunoassay, less than 1% (55 out of 8113) of patients treated with denosumab for up to 5 years tested positive for binding antibodies (including pre-existing, transient, and developing antibodies). None of the patients tested positive for neutralizing antibodies, as was assessed using a chemiluminescent cell-based in vitro biological assay.

There was no identified clinically significant effect of anti-drug antibodies on pharmacokinetics, pharmacodynamics, safety, or effectiveness of denosumab.

13 NONCLINICAL TOXICOLOGY

13.1 Carcinogenesis, Mutagenesis, Impairment of Fertility

Carcinogenicity

The carcinogenic potential of denosumab products has not been evaluated in long-term animal studies.

Mutagenicity

The genotoxic potential of denosumab products has not been evaluated.

Impairment of Fertility

Denosumab had no effect on female fertility or male reproductive organs in monkeys at doses that were 13- to 50-fold higher than the recommended human dose of 60 mg subcutaneously administered once every 6 months, based on body weight (mg/kg).

13.2 Animal Toxicology and/or Pharmacology

Denosumab products are inhibitors of osteoclastic bone resorption via inhibition of RANKL.

In ovariectomized monkeys, once-monthly treatment with denosumab suppressed bone turnover and increased BMD and strength of cancellous and cortical bone at doses 50-fold higher than the recommended human dose of 60 mg administered once every 6 months, based on body weight (mg/kg). Bone tissue was normal with no evidence of mineralization defects, accumulation of osteoid, or woven bone.

Because the biological activity of denosumab in animals is specific to nonhuman primates, evaluation of genetically engineered (“knockout”) mice or use of other biological inhibitors of the RANK/RANKL pathway, namely OPG-Fc, provided additional information on the pharmacodynamic properties of denosumab products. RANK/RANKL knockout mice exhibited absence of lymph node formation, as well as an absence of lactation due to inhibition of mammary gland maturation (lobulo-alveolar gland development during pregnancy). Neonatal RANK/RANKL knockout mice exhibited reduced bone growth and lack of tooth eruption. A corroborative study in 2-week-old rats given the RANKL inhibitor OPG-Fc also showed reduced bone growth, altered growth plates, and impaired tooth eruption. These changes were partially reversible in this model when dosing with the RANKL inhibitors was discontinued.

14 CLINICAL STUDIES

14.1 Treatment of Postmenopausal Women with Osteoporosis

The efficacy and safety of denosumab in the treatment of postmenopausal osteoporosis was demonstrated in a 3-year, randomized, double-blind, placebo-controlled trial. Enrolled women had a baseline BMD T-score between -2.5 and -4.0 at either the lumbar spine or total hip. Women with other diseases (such as rheumatoid arthritis, osteogenesis imperfecta, and Paget's disease) or on therapies that affect bone were excluded from this study. The 7808 enrolled women were aged 60 to 91 years with a mean age of 72 years. Overall, the mean baseline lumbar spine BMD T-score was -2.8, and 23% of women had a vertebral fracture at baseline. Women were randomized to receive subcutaneous injections of either placebo (N = 3906) or denosumab 60 mg (N = 3902) once every 6 months. All women received at least 1000 mg calcium and 400 IU vitamin D supplementation daily.

The primary efficacy variable was the incidence of new morphometric (radiologically-diagnosed) vertebral fractures at 3 years. Vertebral fractures were diagnosed based on lateral spine radiographs (T4-L4) using a semiquantitative scoring method. Secondary efficacy variables included the incidence of hip fracture and nonvertebral fracture, assessed at 3 years.

Effect on Vertebral Fractures

Denosumab significantly reduced the incidence of new morphometric vertebral fractures at 1, 2, and 3 years (p < 0.0001), as shown in Table 3. The incidence of new vertebral fractures at year 3 was 7.2% in the placebo-treated women compared to 2.3% for the denosumab-treated women. The absolute risk reduction was 4.8% and relative risk reduction was 68% for new morphometric vertebral fractures at year 3.

Table 3. The Effect of Denosumab on the Incidence of New Vertebral Fractures in Postmenopausal Women
 | Proportion of Women with Fracture (%)^+ |  | Absolute Risk Reduction (%)* (95% CI) | Relative Risk Reduction (%)* (95% CI)
 | Placebo N = 3691 (%) | Denosumab N = 3702 (%) | Absolute Risk Reduction (%)* (95% CI) | Relative Risk Reduction (%)* (95% CI)
0-1 Year | 2.2 | 0.9 | 1.4 (0.8, 1.9) | 61 (42, 74)
0-2 Years | 5.0 | 1.4 | 3.5 (2.7, 4.3) | 71 (61, 79)
0-3 Years | 7.2 | 2.3 | 4.8 (3.9, 5.8) | 68 (59, 74)
^+ Event rates based on crude rates in each interval.
* Absolute risk reduction and relative risk reduction based on Mantel-Haenszel method adjusting for age group variable.

Denosumab was effective in reducing the risk for new morphometric vertebral fractures regardless of age, baseline rate of bone turnover, baseline BMD, baseline history of fracture, or prior use of a drug for osteoporosis.

Effect on Hip Fractures

The incidence of hip fracture was 1.2% for placebo-treated women compared to 0.7% for denosumab-treated women at year 3. The age-adjusted absolute risk reduction of hip fractures was 0.3% with a relative risk reduction of 40% at 3 years (p = 0.04) (Figure 1).

Figure 1. Cumulative Incidence of Hip Fractures Over 3 Years

N = number of subjects randomized

Effect on Nonvertebral Fractures

Treatment with denosumab resulted in a significant reduction in the incidence of nonvertebral fractures (Table 4).

Table 4. The Effect of Denosumab on the Incidence of Nonvertebral Fractures at Year 3
 | Proportion of Women with Fracture (%)^+ |  | Absolute Risk Reduction (%) (95% CI) | Relative Risk Reduction (%) (95% CI)
 | Placebo N = 3906 (%) | Denosumab N = 3902 (%) | Absolute Risk Reduction (%) (95% CI) | Relative Risk Reduction (%) (95% CI)
Nonvertebral fracture^1 | 8.0 | 6.5 | 1.5 (0.3, 2.7) | 20 (5, 33)*
^+ Event rates based on Kaplan-Meier estimates at 3 years.
^1 Excluding those of the vertebrae (cervical, thoracic, and lumbar), skull, facial, mandible, metacarpus, and finger and toe phalanges.
* p-value = 0.01.

Effect on Bone Mineral Density (BMD)

Treatment with denosumab significantly increased BMD at all anatomic sites measured at 3 years. The treatment differences in BMD at 3 years were 8.8% at the lumbar spine, 6.4% at the total hip, and 5.2% at the femoral neck. Consistent effects on BMD were observed at the lumbar spine, regardless of baseline age, race, weight/body mass index (BMI), baseline BMD, and level of bone turnover.

After denosumab discontinuation, BMD returned to approximately baseline levels within 12 months.

Bone Histology and Histomorphometry

A total of 115 transiliac crest bone biopsy specimens were obtained from 92 postmenopausal women with osteoporosis at either month 24 and/or month 36 (53 specimens in denosumab group, 62 specimens in placebo group). Of the biopsies obtained, 115 (100%) were adequate for qualitative histology and 7 (6%) were adequate for full quantitative histomorphometry assessment.

Qualitative histology assessments showed normal architecture and quality with no evidence of mineralization defects, woven bone, or marrow fibrosis in patients treated with denosumab.

The presence of double tetracycline labeling in a biopsy specimen provides an indication of active bone remodeling, while the absence of tetracycline label suggests suppressed bone formation. In patients treated with denosumab, 35% had no tetracycline label present at the month 24 biopsy and 38% had no tetracycline label present at the month 36 biopsy, while 100% of placebo-treated patients had double label present at both time points. When compared to placebo, treatment with denosumab resulted in virtually absent activation frequency and markedly reduced bone formation rates. However, the long-term consequences of this degree of suppression of bone remodeling are unknown.

14.2 Treatment to Increase Bone Mass in Men with Osteoporosis

The efficacy and safety of denosumab in the treatment to increase bone mass in men with osteoporosis was demonstrated in a 1-year, randomized, double-blind, placebo-controlled trial. Enrolled men had a baseline BMD T-score between -2.0 and -3.5 at the lumbar spine or femoral neck. Men with a BMD T-score between -1.0 and -3.5 at the lumbar spine or femoral neck were also enrolled if there was a history of prior fragility fracture. Men with other diseases (such as rheumatoid arthritis, osteogenesis imperfecta, and Paget's disease) or on therapies that may affect bone were excluded from this study. The 242 men enrolled in the study ranged in age from 31 to 84 years with a mean age of 65 years. Men were randomized to receive SC injections of either placebo (n = 121) or denosumab 60 mg (n = 121) once every 6 months. All men received at least 1000 mg calcium and at least 800 IU vitamin D supplementation daily.

Effect on Bone Mineral Density (BMD)

The primary efficacy variable was percent change in lumbar spine BMD from baseline to 1-year. Secondary efficacy variables included percent change in total hip, and femoral neck BMD from baseline to 1-year.

Treatment with denosumab significantly increased BMD at 1-year. The treatment differences in BMD at 1-year were 4.8% (+0.9% placebo, +5.7% denosumab; (95% CI: 4.0, 5.6); p < 0.0001) at the lumbar spine, 2.0% (+0.3% placebo, +2.4% denosumab) at the total hip, and 2.2% (0.0% placebo, +2.1% denosumab) at femoral neck. Consistent effects on BMD were observed at the lumbar spine regardless of baseline age, race, BMD, testosterone concentrations, and level of bone turnover.

Bone Histology and Histomorphometry

A total of 29 transiliac crest bone biopsy specimens were obtained from men with osteoporosis at 12 months (17 specimens in denosumab group, 12 specimens in placebo group). Of the biopsies obtained, 29 (100%) were adequate for qualitative histology and, in denosumab patients, 6 (35%) were adequate for full quantitative histomorphometry assessment. Qualitative histology assessments showed normal architecture and quality with no evidence of mineralization defects, woven bone, or marrow fibrosis in patients treated with denosumab. The presence of double tetracycline labeling in a biopsy specimen provides an indication of active bone remodeling, while the absence of tetracycline label suggests suppressed bone formation. In patients treated with denosumab, 6% had no tetracycline label present at the month 12 biopsy, while 100% of placebo-treated patients had double label present. When compared to placebo, treatment with denosumab resulted in markedly reduced bone formation rates. However, the long-term consequences of this degree of suppression of bone remodeling are unknown.

14.3 Treatment of Glucocorticoid-Induced Osteoporosis

The efficacy and safety of denosumab in the treatment of patients with glucocorticoid-induced osteoporosis was assessed in the 12-month primary analysis of a 2-year, randomized, multicenter, double-blind, parallel-group, active-controlled study (NCT 01575873) of 795 patients (70% women and 30% men) aged 20 to 94 years (mean age of 63 years) treated with greater than or equal to 7.5 mg/day oral prednisone (or equivalent) for < 3 months prior to study enrollment and planning to continue treatment for a total of at least 6 months (glucocorticoid-initiating subpopulation; n = 290) or ≥ 3 months prior to study enrollment and planning to continue treatment for a total of at least 6 months (glucocorticoid-continuing subpopulation, n = 505). Enrolled patients < 50 years of age were required to have a history of osteoporotic fracture. Enrolled patients ≥ 50 years of age who were in the glucocorticoid-continuing subpopulation were required to have a baseline BMD T-score of ≤ -2.0 at the lumbar spine, total hip, or femoral neck; or a BMD T-score ≤ -1.0 at the lumbar spine, total hip, or femoral neck and a history of osteoporotic fracture.

Patients were randomized (1:1) to receive either an oral daily bisphosphonate (active-control, risedronate 5 mg once daily) (n = 397) or denosumab 60 mg subcutaneously once every 6 months (n = 398) for one year. Randomization was stratified by gender within each subpopulation. Patients received at least 1000 mg calcium and 800 IU vitamin D supplementation daily.

Effect on Bone Mineral Density (BMD)

In the glucocorticoid-initiating subpopulation, denosumab significantly increased lumbar spine BMD compared to the active-control at one year (Active-control 0.8%, denosumab 3.8%) with a treatment difference of 2.9% (p < 0.001). In the glucocorticoid-continuing subpopulation, denosumab significantly increased lumbar spine BMD compared to active-control at one year (Active-control 2.3%, denosumab 4.4%) with a treatment difference of 2.2% (p < 0.001). Consistent effects on lumbar spine BMD were observed regardless of gender; race; geographic region; menopausal status; and baseline age, lumbar spine BMD T-score, and glucocorticoid dose within each subpopulation.

Bone Histology

Bone biopsy specimens were obtained from 17 patients (11 in the active-control treatment group and 6 in the denosumab treatment group) at Month 12. Of the biopsies obtained, 17 (100%) were adequate for qualitative histology. Qualitative assessments showed bone of normal architecture and quality without mineralization defects or bone marrow abnormality. The presence of double tetracycline labeling in a biopsy specimen provides an indication of active bone remodeling, while the absence of tetracycline label suggests suppressed bone formation. In patients treated with active-control, 100% of biopsies had tetracycline label. In patients treated with denosumab, 1 (33%) had tetracycline label and 2 (67%) had no tetracycline label present at the 12-month biopsy. Evaluation of full quantitative histomorphometry including bone remodeling rates was not possible in the glucocorticoid-induced osteoporosis population treated with denosumab. The long-term consequences of this degree of suppression of bone remodeling in glucocorticoid-treated patients is unknown.

14.4 Treatment of Bone Loss in Men with Prostate Cancer

The efficacy and safety of denosumab in the treatment of bone loss in men with nonmetastatic prostate cancer receiving androgen deprivation therapy (ADT) were demonstrated in a 3-year, randomized (1:1), double-blind, placebo-controlled, multinational study. Men less than 70 years of age had either a BMD T-score at the lumbar spine, total hip, or femoral neck between -1.0 and -4.0, or a history of an osteoporotic fracture. The mean baseline lumbar spine BMD T-score was -0.4, and 22% of men had a vertebral fracture at baseline. The 1468 men enrolled ranged in age from 48 to 97 years (median 76 years). Men were randomized to receive subcutaneous injections of either placebo (n = 734) or denosumab 60 mg (n = 734) once every 6 months for a total of 6 doses. Randomization was stratified by age (< 70 years vs. ≥ 70 years) and duration of ADT at trial entry (≤ 6 months vs. > 6 months). Seventy-nine percent of patients received ADT for more than 6 months at study entry. All men received at least 1000 mg calcium and 400 IU vitamin D supplementation daily.

Effect on Bone Mineral Density (BMD)

The primary efficacy variable was percent change in lumbar spine BMD from baseline to month 24. An additional key secondary efficacy variable was the incidence of new vertebral fracture through month 36 diagnosed based on x-ray evaluation by two independent radiologists. Lumbar spine BMD was higher at 2 years in denosumab -treated patients as compared to placebo-treated patients [-1.0% placebo, +5.6% denosumab; treatment difference 6.7% (95% CI: 6.2, 7.1); p < 0.0001].

With approximately 62% of patients followed for 3 years, treatment differences in BMD at 3 years were 7.9% (-1.2% placebo, +6.8% denosumab) at the lumbar spine, 5.7% (-2.6% placebo, +3.2% denosumab) at the total hip, and 4.9% (-1.8% placebo, +3.0% denosumab) at the femoral neck. Consistent effects on BMD were observed at the lumbar spine in relevant subgroups defined by baseline age, BMD, and baseline history of vertebral fracture.

Effect on Vertebral Fractures

Denosumab significantly reduced the incidence of new vertebral fractures at 3 years (p = 0.0125), as shown in Table 5.

Table 5. The Effect of Denosumab on the Incidence of New Vertebral Fractures in Men with Nonmetastatic Prostate Cancer
 | Proportion of Men with Fracture (%)^+ |  | Absolute Risk Reduction (%)* (95% CI) | Relative Risk Reduction (%)* (95% CI)
 | Placebo N = 673 (%) | Denosumab N = 679 (%) | Absolute Risk Reduction (%)* (95% CI) | Relative Risk Reduction (%)* (95% CI)
0-1 Year | 1.9 | 0.3 | 1.6 (0.5, 2.8) | 85 (33, 97)
0-2 Years | 3.3 | 1.0 | 2.2 (0.7, 3.8) | 69 (27, 86)
0-3 Years | 3.9 | 1.5 | 2.4 (0.7, 4.1) | 62 (22, 81)
^+ Event rates based on crude rates in each interval.
* Absolute risk reduction and relative risk reduction based on Mantel-Haenszel method adjusting for age group and ADT duration variables.

14.5 Treatment of Bone Loss in Women with Breast Cancer

The efficacy and safety of denosumab in the treatment of bone loss in women receiving adjuvant aromatase inhibitor (AI) therapy for breast cancer was assessed in a 2-year, randomized (1:1), double-blind, placebo-controlled, multinational study. Women had baseline BMD T-scores between -1.0 to -2.5 at the lumbar spine, total hip, or femoral neck, and had not experienced fracture after age 25. The mean baseline lumbar spine BMD T-score was -1.1, and 2.0% of women had a vertebral fracture at baseline. The 252 women enrolled ranged in age from 35 to 84 years (median 59 years). Women were randomized to receive subcutaneous injections of either placebo (n = 125) or denosumab 60 mg (n = 127) once every 6 months for a total of 4 doses. Randomization was stratified by duration of adjuvant AI therapy at trial entry (≤ 6 months vs. > 6 months). Sixty-two percent of patients received adjuvant AI therapy for more than 6 months at study entry. All women received at least 1000 mg calcium and 400 IU vitamin D supplementation daily.

Effect on Bone Mineral Density (BMD)

The primary efficacy variable was percent change in lumbar spine BMD from baseline to month 12. Lumbar spine BMD was higher at 12 months in denosumab -treated patients as compared to placebo-treated patients [-0.7% placebo, +4.8% denosumab; treatment difference 5.5% (95% CI: 4.8, 6.3); p < 0.0001].

With approximately 81% of patients followed for 2 years, treatment differences in BMD at 2 years were 7.6% (-1.4% placebo, +6.2% denosumab) at the lumbar spine, 4.7 % (-1.0% placebo, +3.8% denosumab) at the total hip, and 3.6% (-0.8% placebo, +2.8% denosumab) at the femoral neck.

16 HOW SUPPLIED/STORAGE AND HANDLING

How Supplied

Conexxence (denosumab-bnht) injection is a clear, colorless to pale yellow solution in a single-dose prefilled syringe with an automatic clear needle safety guard.

60 mg/mL in a single-dose prefilled syringe | 1 per carton | NDC 6521966801

Storage and Handling

Store Conexxence refrigerated at 2°C to 8°C (36°F to 46°F) in the original carton to protect from light. Do not freeze. Prior to administration, Conexxence may be allowed to reach room temperature up to 25°C (77°F) in the original container. Once removed from the refrigerator, Conexxence must not be exposed to temperatures above 25°C (77°F) and must be used within 14 days. Discard Conexxence if not used within 14 days. Do not use Conexxence after the expiry date printed on the label.

Protect Conexxence from direct light and heat.

Avoid vigorous shaking of Conexxence.

17 PATIENT COUNSELING INFORMATION

Advise the patient to read the FDA-approved patient labeling (Medication Guide).

Hypocalcemia

Advise the patient to adequately supplement with calcium and vitamin D and instruct them on the importance of maintaining serum calcium levels while receiving Conexxence [see Warnings and Precautions (5.1), Use in Specific Populations (8.6)]. Advise patients to seek prompt medical attention if they develop signs or symptoms of hypocalcemia.

Severe Hypocalcemia in Patients with Advanced Chronic Kidney Disease

Advise patients with advanced chronic kidney disease, including those who are dialysis-dependent, about the symptoms of hypocalcemia and the importance of maintaining serum calcium levels with adequate calcium and activated vitamin D supplementation. Advise these patients to have their serum calcium measured weekly for the first month after Conexxence administration and monthly thereafter [see Dosage and Administration (2.2), Warnings and Precautions (5.1), Use in Specific Populations (8.6)].

Drug Products with Same Active Ingredient

Advise patients that if they receive Conexxence, they should not receive other denosumab products concomitantly [see Warnings and Precautions (5.2)].

Hypersensitivity

Advise patients to seek prompt medical attention if signs or symptoms of hypersensitivity reactions occur. Advise patients who have had signs or symptoms of systemic hypersensitivity reactions that they should not receive denosumab products [see Warnings and Precautions (5.3), Contraindications (4)].

Osteonecrosis of the Jaw

Advise patients to maintain good oral hygiene during treatment with Conexxence and to inform their dentist prior to dental procedures that they are receiving Conexxence. Patients should inform their physician or dentist if they experience persistent pain and/or slow healing of the mouth or jaw after dental surgery [see Warnings and Precautions (5.4)].

Atypical Subtrochanteric and Diaphyseal Femoral Fractures

Advise patients to report new or unusual thigh, hip, or groin pain [see Warnings and Precautions (5.5)].

Multiple Vertebral Fractures (MVF) Following Treatment Discontinuation

Advise patients not to interrupt Conexxence therapy without talking to their physician [see Warnings and Precautions (5.6)].

Serious Infections

Advise patients to seek prompt medical attention if they develop signs or symptoms of infections, including cellulitis [see Warnings and Precautions (5.7)].

Dermatologic Adverse Reactions

Advise patients to seek prompt medical attention if they develop signs or symptoms of dermatological reactions (such as dermatitis, rashes, and eczema) [see Warnings and Precautions (5.8)].

Musculoskeletal Pain

Inform patients that severe bone, joint, and/or muscle pain have been reported in patients taking denosumab products. Patients should report severe symptoms if they develop [see Warnings and Precautions (5.9)].

Pregnancy/Nursing

Counsel females of reproductive potential to use effective contraceptive measure to prevent pregnancy during treatment and for at least 5 months after the last dose of Conexxence. Advise the patient to contact their physician immediately if pregnancy does occur during these times. Advise patients not to take Conexxence while pregnant or breastfeeding. If a patient wishes to start breastfeeding after treatment, advise her to discuss the appropriate timing with her physician [see Contraindications (4), Use in Specific Populations (8.1)].

Schedule of Administration

Advise patients that if a dose of Conexxence is missed, the injection should be administered as soon as convenient. Thereafter, schedule injections every 6 months from the date of the last injection.

Conexxence (denosumab-bnht)

Manufactured by:
Fresenius Kabi USA, LLC
Lake Zurich, IL 60047, U.S.A

U.S. License No. 2146

Prolia® is a registered trademark of Amgen Inc.

MEDICATION GUIDE
Conexxence (kon ex' ens)
(denosumab-bnht)
Injection, for subcutaneous use

What is the most important information I should know about Conexxence?
If you receive Conexxence, you should not receive other denosumab products at the same time.
Conexxence can cause serious side effects including:

- Increased risk of severe low calcium levels in your blood (hypocalcemia). Conexxence may lower the calcium levels in your blood. If you have low blood calcium before you start receiving Conexxence, it may get worse during treatment. Your low blood calcium must be treated before you receive Conexxence. Talk to your doctor before starting Conexxence. Your doctor may prescribe calcium and vitamin D to help prevent low calcium levels in your blood while you take Conexxence. Take calcium and vitamin D as your doctor tells you to.
  If you have advanced chronic kidney disease (may or may not be on kidney dialysis), Conexxence may increase your risk for severe low calcium levels in your blood, which could result in hospitalization, life-threatening events and death. A mineral and bone disorder associated with kidney disease called chronic kidney disease-mineral bone disorder (CKD-MBD) may increase your risk for severe low calcium levels in blood. Before you start Conexxence and during treatment, your doctor may need to do certain blood tests to check for CKD-MBD.
  Most people with low blood calcium levels do not have symptoms, but some people may have symptoms. Call your doctor right away if you have symptoms of low blood calcium such as:
  - spasms, twitches, or cramps in your muscles
  - numbness or tingling in your fingers, toes, or around your mouth
- Serious allergic reactions. Serious allergic reactions have happened in people who take denosumab products. Call your doctor or go to your nearest emergency room right away if you have any symptoms of a serious allergic reaction. Symptoms of a serious allergic reaction may include:
  - low blood pressure (hypotension)
  - trouble breathing
  - throat tightness
  - swelling of your face, lips, or tongue
  - rash
  - itching
  - hives
- Severe jaw bone problems (osteonecrosis). Severe jaw bone problems may happen when you take Conexxence. Your doctor should examine your mouth before you start Conexxence. Your doctor may tell you to see your dentist before you start Conexxence. It is important for you to practice good mouth care during treatment with Conexxence. Ask your doctor or dentist about good mouth care if you have any questions.
- Unusual thigh bone fractures. Some people have developed unusual fractures in their thigh bone. Symptoms of a fracture include new or unusual pain in your hip, groin, or thigh.
- Increased risk of broken bones, including broken bones in the spine, after stopping, skipping or delaying Conexxence. Talk with your doctor before starting Conexxence treatment. After your treatment with Conexxence is stopped, or if you skip or delay taking a dose, your risk for breaking bones, including bones in your spine, is increased. Your risk for having more than 1 broken bone in your spine is increased if you have already had a broken bone in your spine. Do not stop, skip or delay taking Conexxence without first talking with your doctor. If your Conexxence treatment is stopped, talk to your doctor about other medicine that you can take.
- Serious infections. Serious infections in your skin, lower stomach area (abdomen), bladder, or ear may happen if you take Conexxence. Inflammation of the inner lining of the heart (endocarditis) due to an infection also may happen more often in people who take Conexxence. You may need to go to the hospital for treatment if you develop an infection.
  Conexxence is a medicine that may affect the ability of your body to fight infections. People who have a weakened immune system or take medicines that affect the immune system may have an increased risk for developing serious infections. Call your doctor right away if you have any of the following symptoms of infection:
  - fever or chills
  - skin that looks red or swollen and is hot or tender to touch
  - fever, shortness of breath, cough that will not go away
  - severe abdominal pain
  - frequent or urgent need to urinate or burning feeling when you urinate
- Skin problems. Skin problems such as inflammation of your skin (dermatitis), rash, and eczema may happen if you take Conexxence. Call your doctor if you have any of the following symptoms of skin problems that do not go away or get worse:
  - redness
  - itching
  - small bumps or patches (rash)
  - your skin is dry or feels like leather
  - blisters that ooze or become crusty
  - skin peeling
- Bone, joint, or muscle pain. Some people who take denosumab products develop severe bone, joint, or muscle pain.

Call your doctor right away if you have any of these side effects.

What is Conexxence?
Conexxence is a prescription medicine used to:

- Treat osteoporosis (thinning and weakening of bone) in women after menopause (“change of life”) who:
  - are at high risk for fracture (broken bone)
  - cannot use another osteoporosis medicine or other osteoporosis medicines did not work well
- Increase bone mass in men with osteoporosis who are at high risk for fracture.
- Treat osteoporosis in men and women who will be taking corticosteroid medicines (such as prednisone) for at least 6 months and are at high risk for fracture.
- Treat bone loss in men who are at high risk for fracture receiving certain treatments for prostate cancer that has not spread to other parts of the body.
- Treat bone loss in women who are at high risk for fracture receiving certain treatments for breast cancer that has not spread to other parts of the body.

It is not known if Conexxence is safe and effective in children. Conexxence is not approved for use in children.

Do not take Conexxence if you:

- have been told by your doctor that your blood calcium level is too low.
- are pregnant or plan to become pregnant.
- are allergic to denosumab products or any of the ingredients in Conexxence. See the end of this Medication Guide for a complete list of ingredients in Conexxence.

Before taking Conexxence, tell your doctor about all of your medical conditions, including if you:

- are taking other denosumab products.
- have low blood calcium.
- cannot take daily calcium and vitamin D.
- had parathyroid or thyroid surgery (glands located in your neck).
- have been told you have trouble absorbing minerals in your stomach or intestines (malabsorption syndrome).
- have kidney problems or are on kidney dialysis.
- are taking medicine that can lower your blood calcium levels.
- plan to have dental surgery or teeth removed.
- are pregnant or plan to become pregnant. Conexxence may harm your unborn baby.
  Females who are able to become pregnant:
  - Your healthcare provider should do a pregnancy test before you start treatment with Conexxence.
  - You should use an effective method of birth control (contraception) during treatment with Conexxence and for at least 5 months after your last dose of Conexxence.
  - Tell your doctor right away if you become pregnant while taking Conexxence.
- are breastfeeding or plan to breastfeed. It is not known if Conexxence passes into your breast milk. You and your doctor should decide if you will take Conexxence or breastfeed. You should not do both.

Tell your doctor about all the medicines you take, including prescription and over-the-counter medicines, vitamins, and herbal supplements.
Know the medicines you take. Keep a list of medicines with you to show to your doctor or pharmacist when you get a new medicine.

How will I receive Conexxence?

- Conexxence is an injection that will be given to you by a healthcare provider. Conexxence is injected under your skin (subcutaneous).
- You will receive Conexxence 1 time every 6 months.
- You should take calcium and vitamin D as your doctor tells you to while you receive Conexxence.
- If you miss a dose of Conexxence, you should receive your injection as soon as you can.
- Take good care of your teeth and gums while you receive Conexxence. Brush and floss your teeth regularly.
- Tell your dentist that you are receiving Conexxence before you have dental work.

What are the possible side effects of Conexxence?
Conexxence may cause serious side effects.

- See “What is the most important information I should know about Conexxence?”
- It is not known if the use of Conexxence over a long period of time may cause slow healing of broken bones.

The most common side effects of Conexxence in women who are being treated for osteoporosis after menopause are:

- back pain
- pain in your arms and legs
- high cholesterol

- muscle pain
- bladder infection

The most common side effects of Conexxence in men with osteoporosis are:

- back pain
- joint pain

- common cold (runny nose or sore throat)

The most common side effects of Conexxence in patients with glucocorticoid-induced osteoporosis are:

- back pain
- high blood pressure

- lung infection (bronchitis)
- headache

The most common side effects of Conexxence in patients receiving certain treatments for prostate or breast cancer are:

- joint pain
- back pain

- pain in your arms and legs
- muscle pain

Tell your doctor if you have any side effect that bothers you or that does not go away.
These are not all the possible side effects of Conexxence.
Call your doctor for medical advice about side effects. You may report side effects to FDA at 1-800-FDA-1088.

How should I store Conexxence if I need to pick it up from a pharmacy?

- Keep Conexxence in a refrigerator at 36°F to 46°F (2°C to 8°C) in the original carton.
- Do not freeze Conexxence.
- When you remove Conexxence from the refrigerator, Conexxence must be kept at room temperature [up to 77°F (25°C)] in the original carton and must be used within 14 days.
- Do not keep Conexxence at temperatures above 77°F (25°C). Warm temperatures will affect how Conexxence works.
- Do not shake Conexxence.
- Keep Conexxence in the original carton to protect from light.

Keep Conexxence and all medicines out of the reach of children.

General information about the safe and effective use of Conexxence.
Medicines are sometimes prescribed for purposes other than those listed in a Medication Guide. Do not use Conexxence for a condition for which it was not prescribed. Do not give Conexxence to other people, even if they have the same symptoms that you have. It may harm them. You can ask your doctor or pharmacist for information about Conexxence that is written for healthcare providers.

What are the ingredients in Conexxence?
Active ingredient: denosumab-bnht
Inactive ingredients: glacial acetic acid, polysorbate 20, sodium acetate, sorbitol, and Water for Injection (USP). Sodium hydroxide may be added to adjust pH.

Fresenius Kabi USA, LLC
Lake Zurich, IL 60047, U.S.A
U.S. License No. 2146

This Medication Guide has been approved by the U.S. Food and Drug Administration.

Issued: 03/2025

Principal Display Panel – 60 mg/mL Carton Label

NDC 65219-668-01 Rx only

Scan for additional information

Conexxence
denosumab-bnht
Injection

60 mg/mL

For Subcutaneous use only

Single-dose prefilled syringe.
discard unused portion.

Carton contains:

1 Single-dose prefilled syringe
1 Prescribing Information
1 Medication Guide

Dispense the enclosed Medication
Guide to each patient

Sterile Solution - No Preservative

Conexxence should be administered by a healthcare provider

Fresenius
Kabi

Principal Display Panel – 60 mg/mL Syringe Label

NDC 65219-668-01 Rx only

Conexxence
denosumab-bnht
Injection

60 mg/mL

For Subcutaneous
use only

Fresenius Kabi USA, LLC
U.S. License No. 2146